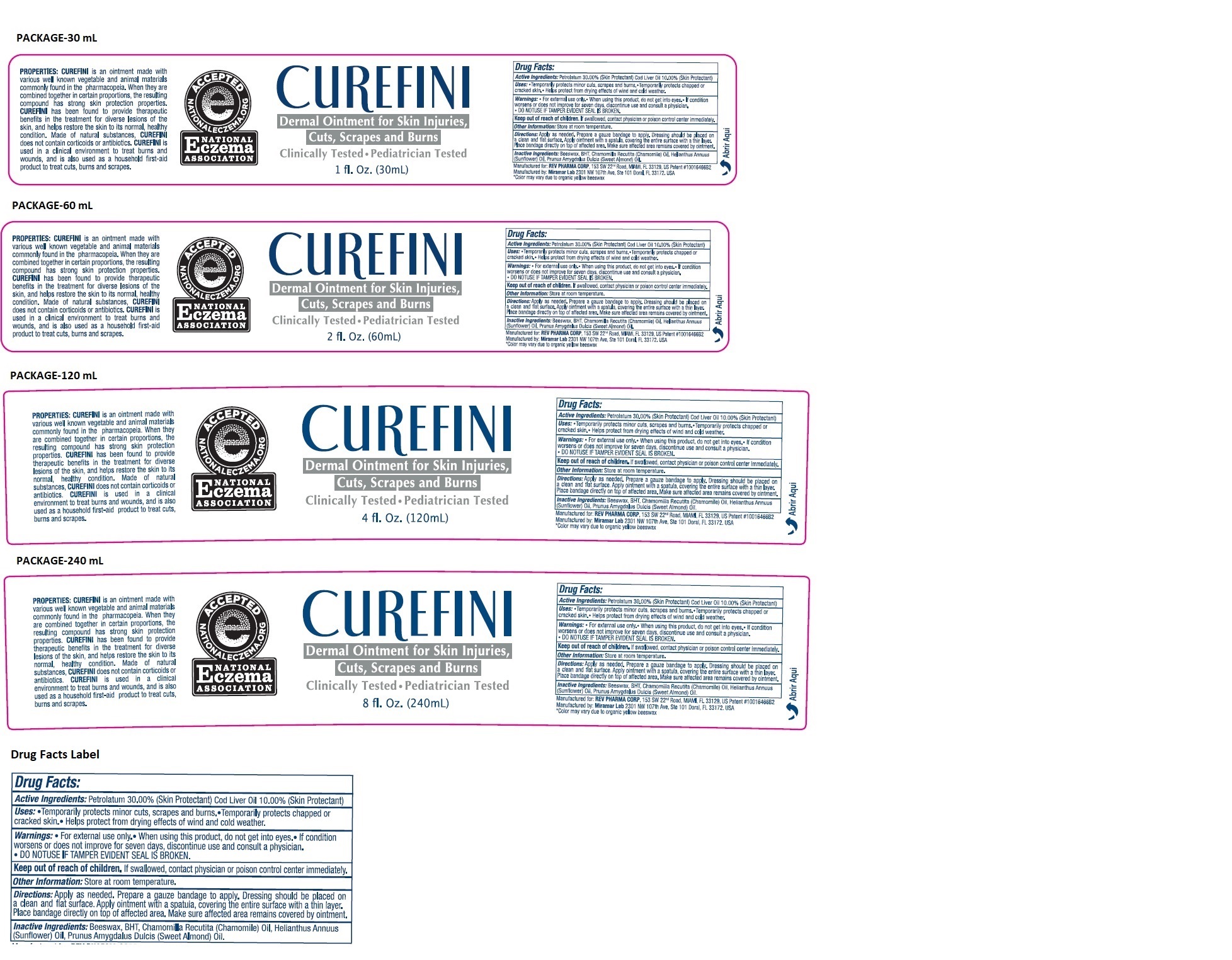 DRUG LABEL: CUREFINI
NDC: 79974-202 | Form: OINTMENT
Manufacturer: Miramar Cosmetics, Inc DBA Miramar Lab
Category: otc | Type: HUMAN OTC DRUG LABEL
Date: 20241223

ACTIVE INGREDIENTS: PETROLATUM 300 mg/1 mL; COD LIVER OIL 100 mg/1 mL
INACTIVE INGREDIENTS: YELLOW WAX; BUTYLATED HYDROXYTOLUENE; CHAMOMILE; HELIANTHUS ANNUUS FLOWERING TOP; ALMOND OIL

CUREFINI

Active Ingredients:

Petrolatum 30.00%
Cod Liver Oil 10.00%

Purpose:

Skin Protectant

Uses:

• Temporarily protects minor cuts, scrapes and burns. • Temporarily protects chapped or cracked skin. • Helps protect from drying effects of wind and cold weather.

Warnings:

• For external use only. • When using this product, do not get into eyes. • If condition worsens or does not improve for seven days, discontinue use and consult a physician.
• DO NOT USE IF TAMPER EVIDENT SEAL IS BROKEN.

Keep out of reach of children. If swallowed, contact physician or poison control center immediately. Other Information: Store at room temperature.

Other Information:

Store at room temperature.

Directions:

Apply as needed. Prepare a gauze bandage to apply. Dressing should be placed on a clean and flat surface. Apply ointment with a spatula, covering the entire surface with a thin layer. Place bandage directly on top of affected area. Make sure affected area remains covered by ointment.

Inactive Ingredients:

Beeswax, BHT, Chamomilla Recutita (Chamomile) Oil, Helianthus Annuus (Sunflower) Oil, Prunus Amygdalus Dulcis (Sweet Almond) Oil.

PROPERTIES: CUREFINI is an ointment made with various well known vegetable and animal materials commonly found in the pharmacopeia. When they are combined together in certain proportions, the resulting compound has strong skin protection properties. CUREFINI has been found to provide therapeutic benefits in the treatment for diverse lesions of the skin, and helps restore the skin to its normal, healthy condition. Made of natural substances, CUREFINI does not contain corticoids or antibiotics. CUREFINI is used in a clinical environment to treat burns and wounds, and is also used as a household first-aid product to treat cuts, burns and scrapes.

Dermal Ointment for Skin Injuries, Cuts, Scrapes and Burns

ACCEPTED NATIONALECZEMA.ORG

NATIONAL ECZEMA ASSOCIATION

Clinically Tested • Pediatrician Tested

Manufactured for: REV PHARMA CORP, 153 SW 22" Road, MIAMI, FL 33129, US Patent #10016466B2
Manufactured by: Miramar Lab 2301 NW 107th Ave, Ste 101 Doral, FL 33172, USA
*Color may vary due to organic yellow beeswax